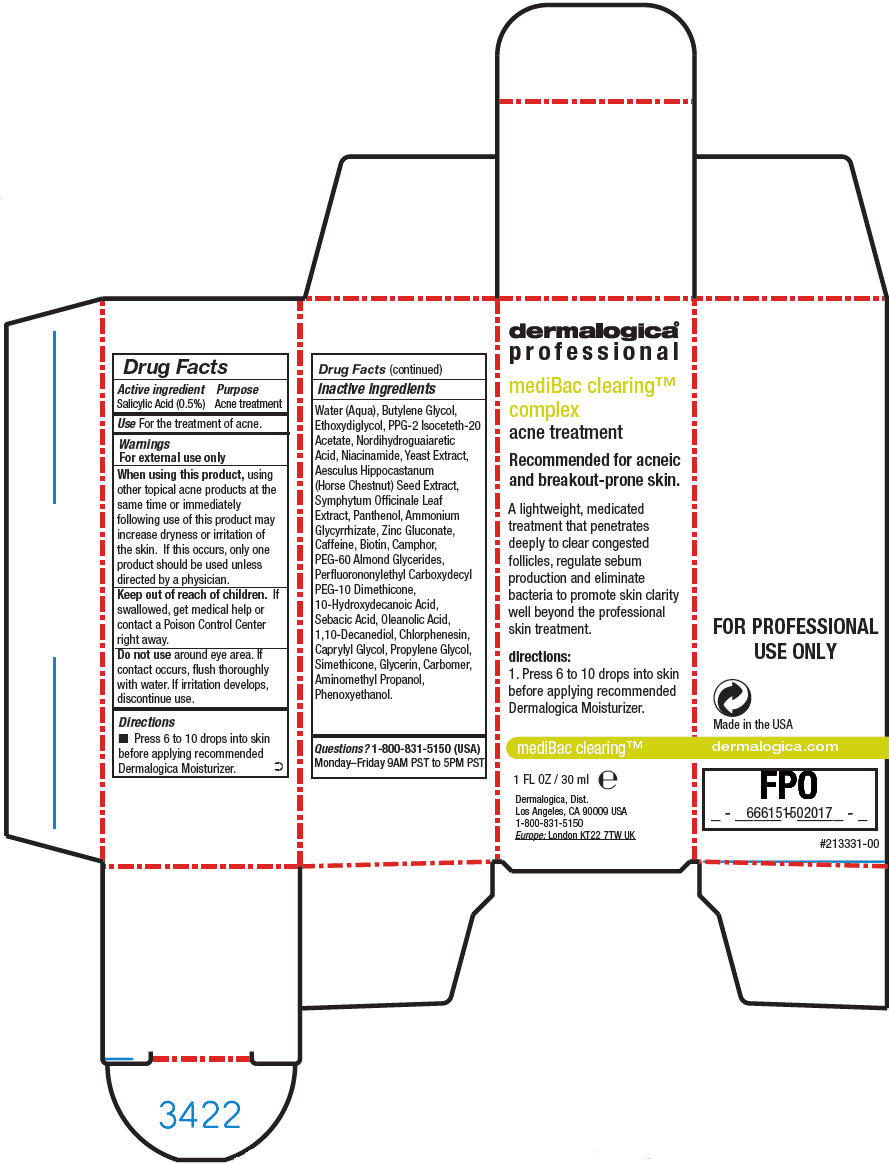 DRUG LABEL: MediBac Clearing Complex
NDC: 68479-804 | Form: LIQUID
Manufacturer: Dermalogica, Inc.
Category: otc | Type: HUMAN OTC DRUG LABEL
Date: 20151124

ACTIVE INGREDIENTS: Salicylic Acid 5 mg/1 mL
INACTIVE INGREDIENTS: Water; Butylene Glycol; Diethylene Glycol Monoethyl Ether; PPG-2 Isoceteth-20 Acetate; Masoprocol; Niacinamide; Yeast, unspecified; Horse Chestnut; Panthenol; Ammonium Glycyrrhizate; Zinc Gluconate; Caffeine; Biotin; Comfrey Leaf; Camphor (Synthetic); PEG-60 Almond Glycerides; 10-Hydroxydecanoic Acid; Sebacic Acid; Oleanolic Acid; 1,10-Decanediol; Chlorphenesin; Caprylyl Glycol; Propylene Glycol; Glycerin; Carbomer Homopolymer Type C (Allyl Pentaerythritol Crosslinked); Aminomethylpropanol; Phenoxyethanol

MediBac Clearing™ Complex

Drug Facts

Active ingredient

Salicylic Acid (0.5%)

Purpose

Acne treatment

Use

For the treatment of acne.

Warnings

For external use only

When using this product, using other topical acne products at the same time or immediately following use of this product may increase dryness or irritation of the skin. If this occurs, only one product should be used unless directed by a physician.

Keep out of reach of children. If swallowed, get medical help or contact a Poison Control Center right away.

Do not use around eye area. If contact occurs, flush thoroughly with water. If irritation develops, discontinue use.

Directions

- Press 6 to 10 drops into skin before applying recommended Dermalogica Moisturizer.

Inactive ingredients

Water (Aqua), Butylene Glycol, Ethoxydiglycol, PPG-2 Isoceteth-20 Acetate, Nordihydroguaiaretic Acid, Niacinamide, Yeast Extract, Aesculus Hippocastanum (Horse Chestnut) Seed Extract, Symphytum Officinale Leaf Extract, Panthenol, Ammonium Glycyrrhizate, Zinc Gluconate, Caffeine, Biotin, Camphor, PEG-60 Almond Glycerides, Perfluorononylethyl Carboxydecyl PEG-10 Dimethicone, 10-Hydroxydecanoic Acid, Sebacic Acid, Oleanolic Acid, 1,10-Decanediol, Chlorphenesin, Caprylyl Glycol, Propylene Glycol, Simethicone, Glycerin, Carbomer, Aminomethyl Propanol, Phenoxyethanol.

Questions?

1-800-831-5150 (USA) Monday–Friday 9AM PST to 5PM PST

PRINCIPAL DISPLAY PANEL - 30 ml Bottle Carton

dermalogica®
professional

mediBac clearing™
complex

acne treatment

Recommended for acneic
and breakout-prone skin.

A lightweight, medicated
treatment that penetrates
deeply to clear congested
follicles, regulate sebum
production and eliminate
bacteria to promote skin clarity
well beyond the professional
skin treatment.

directions:

1. Press 6 to 10 drops into skin
before applying recommended
Dermalogica Moisturizer.

mediBac clearing™

1 FL OZ / 30 ml e

Dermalogica, Dist.
Los Angeles, CA 90009 USA
1-800-831-5150
Europe: London KT22 7TW UK